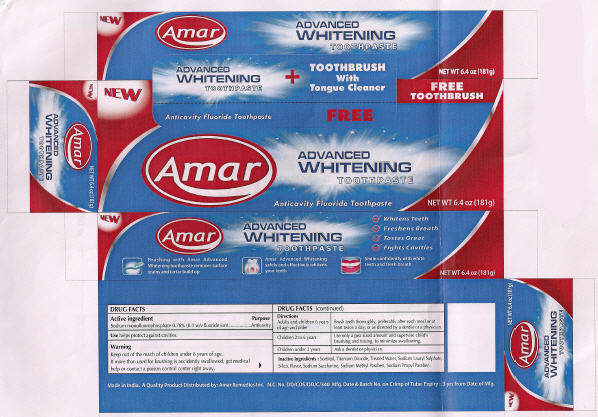 DRUG LABEL: Amar 
NDC: 41499-107 | Form: PASTE, DENTIFRICE
Manufacturer: Amar Remedies Limited - Mumbai
Category: otc | Type: HUMAN OTC DRUG LABEL
Date: 20091222

ACTIVE INGREDIENTS: Sodium Fluoride 0.22 g/100 g
INACTIVE INGREDIENTS: Water; Silicon Dioxide

Amar
ADVANCED
WHITENING
TOOTHPASTE

DRUG FACTS

Active ingredient

Sodium Fluoride 0.22% (0.1 w/v fluoride ion)

Purpose

Anticavity

Use

helps protect against cavities.

Warning

KEEP OUT OF REACH OF CHILDREN

Keep out of the reach of children under 6 years of age.

If more than used for brushing is accidently swallowed, get medical help or contact a poison control center right away.

Directions

Adults and children 6 years of age and older | Brush teeth thoroughly, preferably after each meal or at least twice a day, or as directed by a dentist or a physician.
Children 2 to 6 years | Use only a pea sized amount and supervise child's brushing and rinsing to minimize swallowing.
Children under 2 years | Ask a dentist or physician.

Inactive Ingredients

Sorbitol, Titanium Dioxide, Treated Water, Sodium Lauryl Sulphate, Silica, Flavor, Sodium Saccharine, Sodium Methyl Paraben, Sodium Propyl Paraben, Sodium Carboxymethylcellulose (SCMC).

Distributed by: Amar Remedies Inc.

PRINCIPAL DISPLAY PANEL - 181 g Carton

NEW

Anticavity Fluoride Toothpaste

Amar

FREE Toothbrush

ADVANCED
WHITENING
TOOTHPASTE

Anticavity Fluoride Toothpaste

NET WT 6.4 oz (181g)